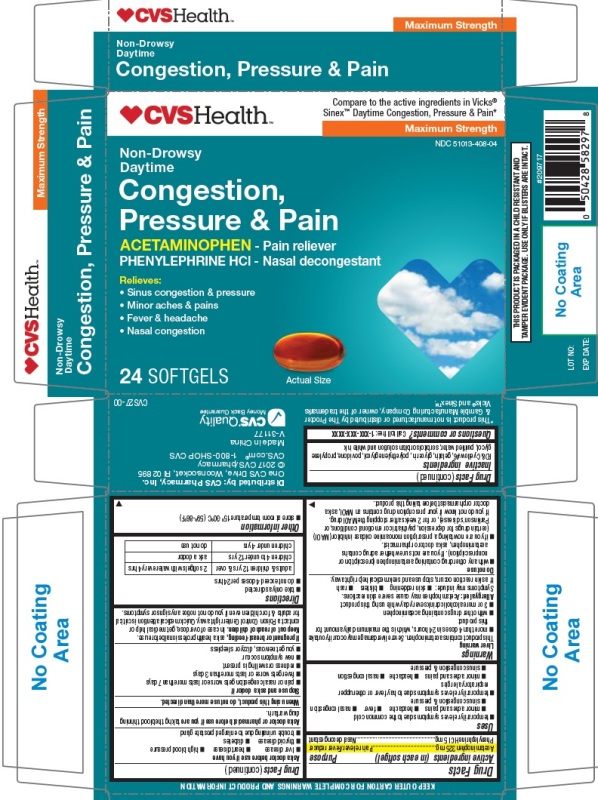 DRUG LABEL: Daytime Congestion Pressure and Pain
NDC: 51013-408 | Form: CAPSULE, LIQUID FILLED
Manufacturer: PuraCap Pharmaceutical LLC
Category: otc | Type: HUMAN OTC DRUG LABEL
Date: 20200103

ACTIVE INGREDIENTS: ACETAMINOPHEN 325 mg/1 1; PHENYLEPHRINE HYDROCHLORIDE 5 mg/1 1
INACTIVE INGREDIENTS: FD&C YELLOW NO. 6; GELATIN; GLYCERIN; POLYETHYLENE GLYCOL, UNSPECIFIED; POVIDONE; PROPYLENE GLYCOL; WATER; SORBITOL; SORBITAN

Daytime Congestion, Pressure & Pain

Active ingredients (in each softgel)

Acetaminophen 325 mg

Phenylephrine HCl 5 mg

Purpose

Pain reliever/Fever reducer

Nasal decongestant

Uses

- temporarily relieves symptoms due to the common cold
  - minor aches and pains
  - headache
  - fever
  - nasal congestion
  - sinus congestion & pressure
- temporarily relieves symptoms due to hay fever or other upper respiratory allergies
  - minor aches and pains
  - headache
  - nasal congestion
  - sinus congestion & pressure

Warnings

Liver warning

This product contains acetaminophen. Severe liver damage may occur if you take

- more than 4 doses in 24 hours, which is the maximum daily amount for this product
- with other drugs containing acetaminophen
- 3 or more alcoholic drinks daily while using this product

Allergy alert: Acetaminophen may cause severe skin reactions. Symptoms may include:

- skin reddening
- blisters
- rash

If a skin reaction occurs, stop use and seek medical help right away.

Do not use

- with any other drug containing acetaminophen (prescription or nonprescription). If you are not sure whether a drug contains acetaminophen, ask a doctor or pharmacist.
- if you are now taking a prescription monoamine oxidase inhibitor (MAOI) (certain drugs for depression, psychiatric or emotional conditions, or Parkinson's disease), or for 2 weeks after stopping the MAOI drug. If you do not know if your prescription drug contains an MAOI, ask a doctor or pharmacist before taking this product.

Ask a doctor before use if you have

- liver disease
- heart disease
- high blood pressure
- thyroid disease
- diabetes
- trouble urinating due to enlarged prostate gland

Ask a doctor or pharmacist before use if you are taking the blood thinning drug warfarin.

When using this product, do not use more than directed.

Stop use and ask a doctor if

- pain or nasal congestion gets worse or lasts more than 7 days
- fever gets worse or lasts more than 3 days
- redness or swelling is present
- new symptoms occur
- you get nervous, dizzy or sleepless

PREGNANCY OR BREAST FEEDING

If pregnant or breast-feeding, ask a health professional before use.

Keep out of reach of children. In case of overdose, get medical help or contact a Poison Control Center right away. Quick medical attention is critical for adults & for children even if you do not notice any signs or symptoms.

Directions

- take only as directed
- do not exceed 4 doses per 24 hrs

adults and children 12 yrs & over | 2 softgels with water every 4 hrs
children 4 to under 12 yrs | ask a doctor
children under 4 yrs | do not use

Other information

- store at room temperature 15°-30°C (59°-86°F)

Inactive ingredients

FD&C yellow #6, gelatin, glycerin, polyethylene glycol, povidone, propylene glycol, purified water, sorbitol sorbitan solution and white ink

Questions or comments?

Call toll free: 1-855-215-8180

PRINCIPAL DISPLAY PANEL

Daytime Congestion, Pressure & Pain 24 SOFTGELS

NDC 51013-408-04

*Compare to the active ingredients in Vicks® Sinex™ Daytime Congestion, Pressure & Pain